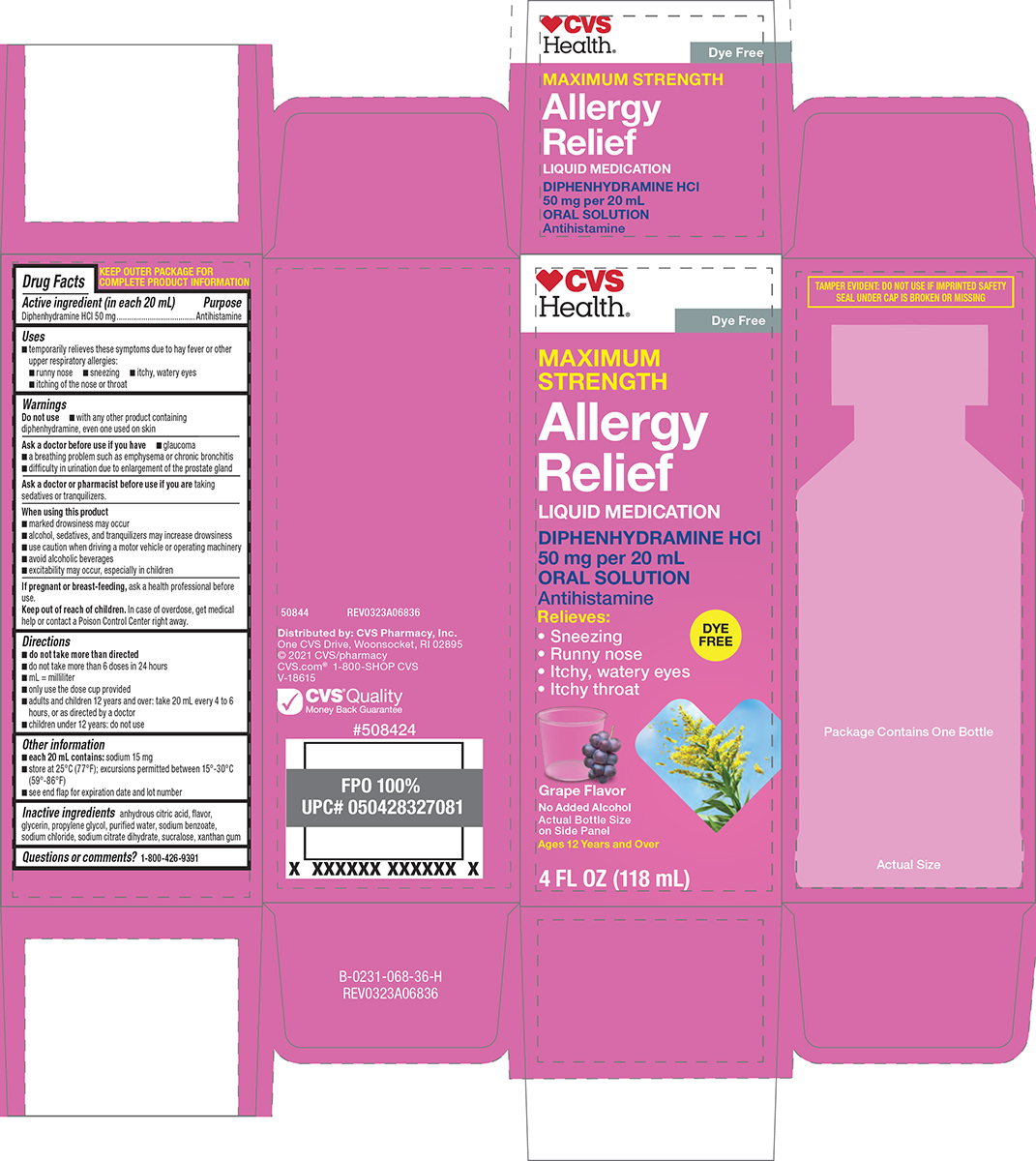 DRUG LABEL: Allergy Relief
NDC: 69842-174 | Form: SOLUTION
Manufacturer: CVS PHARMACY
Category: otc | Type: HUMAN OTC DRUG LABEL
Date: 20250923

ACTIVE INGREDIENTS: DIPHENHYDRAMINE HYDROCHLORIDE 50 mg/20 mL
INACTIVE INGREDIENTS: ANHYDROUS CITRIC ACID; GLYCERIN; PROPYLENE GLYCOL; WATER; SODIUM BENZOATE; SODIUM CHLORIDE; TRISODIUM CITRATE DIHYDRATE; SUCRALOSE; XANTHAN GUM

CVS 44-068

Active ingredient (in each 20 mL)

Diphenhydramine HCl 50 mg

Purpose

Antihistamine

Uses

- temporarily relieves these symptoms due to hay fever or other upper respiratory allergies:
  - runny nose
  - sneezing
  - itchy, watery eyes
  - itching of the nose or throat

Warnings

Do not use

- with any other product containing diphenhydramine, even one used on skin

Ask a doctor before use if you have

- glaucoma
- a breathing problem such as emphysema or chronic bronchitis
- difficulty in urination due to enlargement of the prostate gland

Ask a doctor or pharmacist before use if you are

taking sedatives or tranquilizers.

When using this product

- marked drowsiness may occur
- alcohol, sedatives, and tranquilizers may increase drowsiness
- use caution when driving a motor vehicle or operating machinery
- avoid alcoholic beverages
- excitability may occur, especially in children

If pregnant or breast-feeding,

ask a health professional before use.

Keep out of reach of children.

In case of overdose, get medical help or contact a Poison Control Center right away.

Directions

- do not take more than directed
- do not take more than 6 doses in 24 hours
- mL = milliliter
- only use the dose cup provided
- adults and children 12 years and over: take 20 mL every 4 to 6 hours, or as directed by a doctor
- children under 12 years: do not use

Other information

- each 20 mL contains: sodium 15 mg
- store at 25°C (77°F); excursions permitted between 15°-30°C (59°-86°F)
- see end flap for expiration date and lot number

Inactive ingredients

anhydrous citric acid, flavor, glycerin, propylene glycol, purified water, sodium benzoate, sodium chloride, sodium citrate dihydrate, sucralose, xanthan gum

Questions or comments?

1-800-426-9391

Principal display panel

♥CVS
Health®

Dye Free

MAXIMUM
STRENGTH
Allergy
Relief

LIQUID MEDICATION

DIPHENHYDRAMINE HCI
50 mg per 20 mL
ORAL SOLUTION
Antihistamine

DYE
FREE

Relieves:
• Sneezing
• Runny nose
• Itchy, watery eyes
• Itchy throat

Grape Flavor

No Added Alcohol
Actual Bottle Size
on Side Panel
Ages 12 Years and Over

4 FL OZ (118 mL)

TAMPER EVIDENT: DO NOT USE IF IMPRINTED SAFETY
SEAL UNDER CAP IS BROKEN OR MISSING

Package Contains One Bottle

Actual Size

50844 REV0323A06836

Distributed by: CVS Pharmacy, Inc.
One CVS Drive, Woonsocket, RI 02895
© 2021 CVS/pharmacy
CVS.com® 1-800-SHOP CVS
V-18615

CVS® Quality
Money Back Guarantee

#508424

CVS 44-068